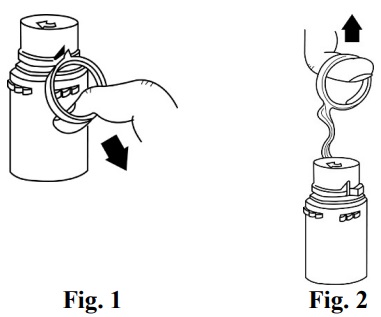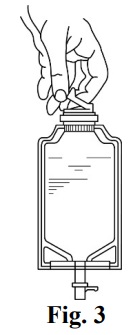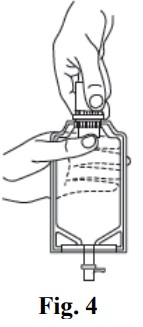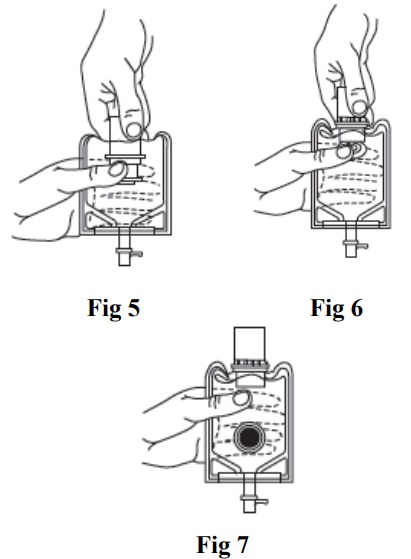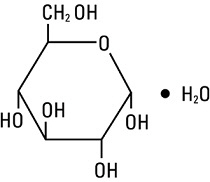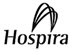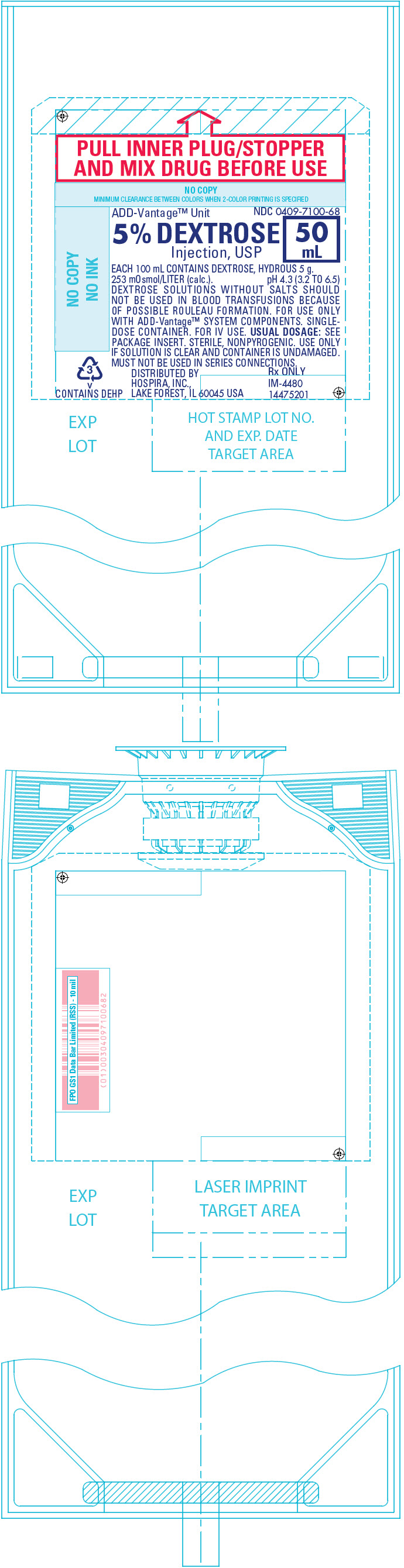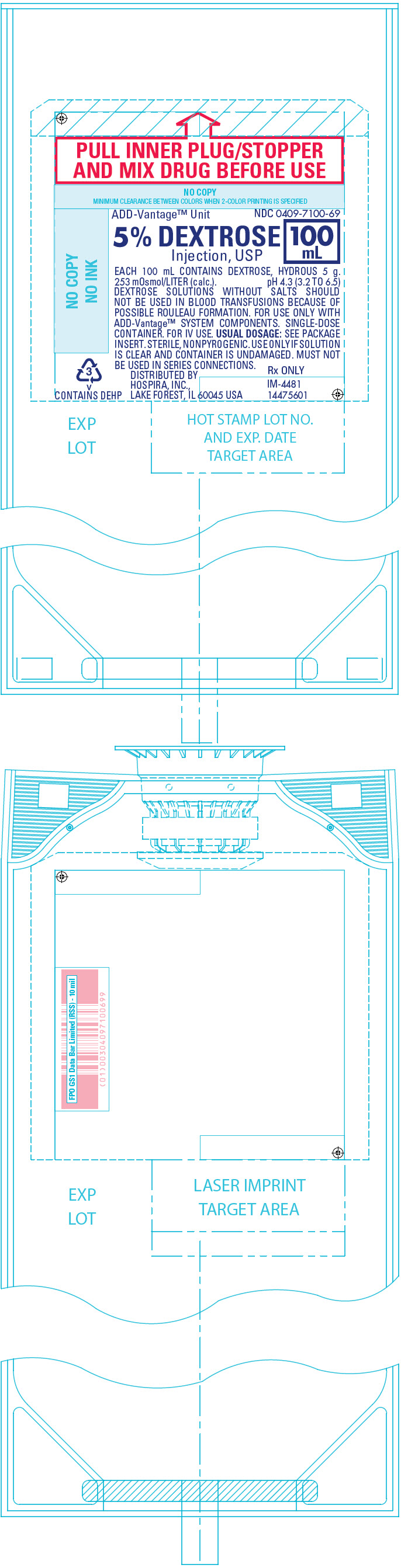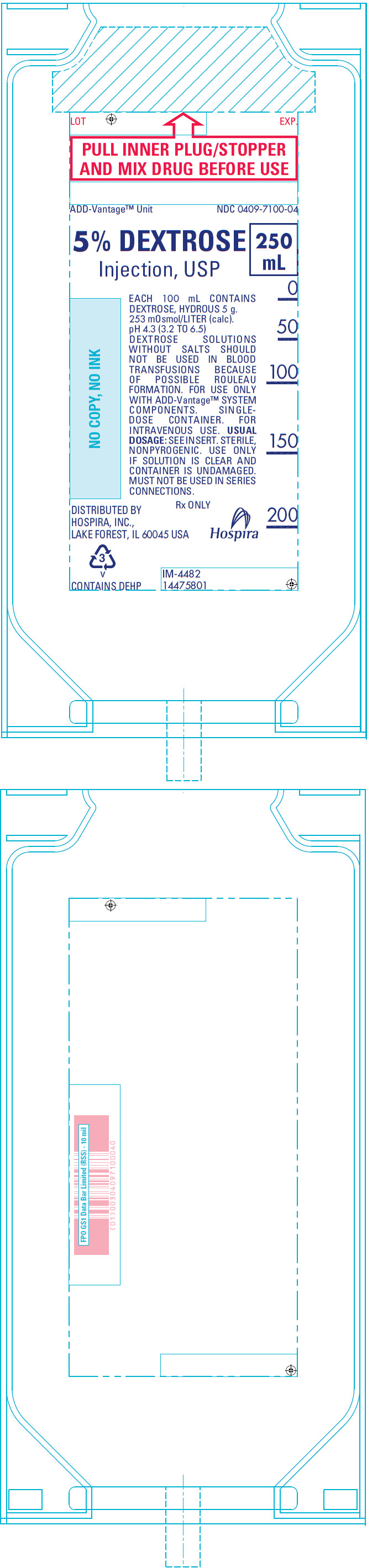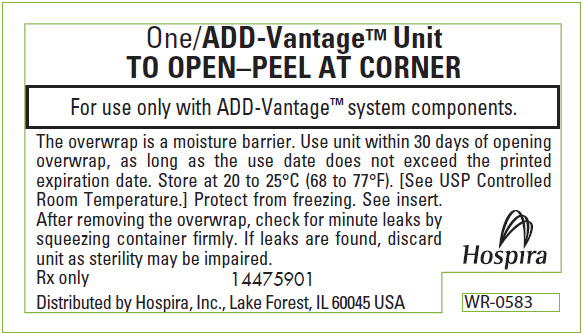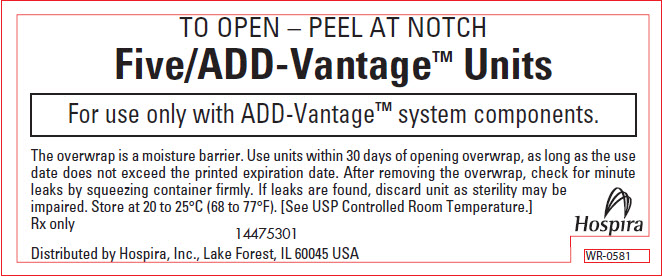 DRUG LABEL: Dextrose
NDC: 0409-7100 | Form: INJECTION, SOLUTION
Manufacturer: Hospira, Inc.
Category: prescription | Type: HUMAN PRESCRIPTION DRUG LABEL
Date: 20250616

ACTIVE INGREDIENTS: DEXTROSE MONOHYDRATE 50 mg/1 mL
INACTIVE INGREDIENTS: WATER

HIGHLIGHTS OF PRESCRIBING INFORMATION

These highlights do not include all the information needed to use DEXTROSE INJECTION (5%) safely and effectively. See full prescribing information for DEXTROSE INJECTION (5%).
DEXTROSE injection, for intravenous use
Initial U.S. Approval: 1940

RECENT MAJOR CHANGES

Dosage and Administration (2.1, 2.2, 2.3) | 06/2025
Contraindications (4) | 06/2025
Warnings and Precautions (5.1, 5.2, 5.3, 5.4, 5.5, 5.6, 5.7) | 06/2025

1 INDICATIONS AND USAGE

Dextrose Injection (5%) is indicated as a source of water and calories in adult and pediatric patients and may also be used as a diluent for reconstitution of a powder or liquid drug product. (1)

2 DOSAGE AND ADMINISTRATION

- Only for intravenous infusion. (2.1)
- Infusion rate depends on the age, weight, clinical, and metabolic conditions of the patient and concomitant therapy. See full prescribing information for more information on preparation, administration, and dosing considerations. (2.1, 2.2, 2.3)

3 DOSAGE FORMS AND STRENGTHS

Injection:

- 5% (5 g/100 mL) (50 mg/mL) of dextrose hydrous in single-dose flexible plastic ADD-VantageTM diluent containers: 50 mL, 100 mL and 250 mL.

This dextrose product is intended to be used as a diluent for the contents of an ADD-Vantage vial or a single-dose powdered drug vial with 20 mm closure using the ADD-Vantage ADDAPTORTM. (3)

4 CONTRAINDICATIONS

- Clinically significant hyperglycemia. (4)
- Known hypersensitivity to dextrose. (4)

5 WARNINGS AND PRECAUTIONS

- Neonatal Hypoglycemia: Closely monitor blood glucose concentration to ensure adequate glycemic control. (5.1)
- Hyperglycemia and Hyperosmolar Hyperglycemic State: Use with caution in patients with known subclinical or overt diabetes mellitus. (5.2)
- Hypersensitivity Reactions: Monitor for signs and symptoms and discontinue infusion immediately if reaction occurs. (5.3)
- Phlebitis and Thrombosis: Remove catheter as soon as possible if thrombophlebitis develops. (2.1, 5.4)
- Hyponatremia: Monitor serum sodium and chloride concentrations, fluid status, acid-base balance, and neurologic status. (5.5)
- Electrolyte Imbalance and Fluid Overload: Monitor changes in fluid balance, electrolyte concentrations, and acid-base balance during administration. (5.6)
- Refeeding Syndrome: Monitory laboratory parameters. (5.7)

6 ADVERSE REACTIONS

The most common adverse reactions are hyperglycemia, hypersensitivity reactions, hyponatremia, infection (both systemic and at the injection site), vein thrombosis, phlebitis, and electrolyte imbalance. (6)

To report SUSPECTED ADVERSE REACTIONS, contact Pfizer, Inc. at 1-800-438-1985 or FDA at 1-800-FDA-1088 or www.fda.gov/medwatch.

7 DRUG INTERACTIONS

Effects on Glycemic Control and Electrolyte Balance: Monitor blood glucose concentrations, fluid balance, serum electrolyte concentrations, and acid-base balance. Avoid use of Dextrose Injection in patients receiving drugs associated with hyponatremia. (7.1)

8 USE IN SPECIFIC POPULATIONS

Pediatric Use: Increased risk of hypoglycemia/hyperglycemia and imbalances in fluid/electrolytes; monitor serum glucose concentrations, volume status, and electrolytes. (8.4)

FULL PRESCRIBING INFORMATION

1 INDICATIONS AND USAGE

Dextrose Injection (5%) is indicated as a source of water and calories in adult and pediatric patients and may also be used as a diluent for reconstitution of a powder or liquid drug product.

2 DOSAGE AND ADMINISTRATION

2.1 Important Administration Instructions

Dextrose Injection (5%) is intended for intravenous use.

- Use a peripheral vein to administer if the final dextrose concentration is 5% or less and the osmolarity is less than 900 mOsm/L.
- To avoid venous irritation, consider using a central vein to administer hypertonic solutions with osmolarity of 900 mOsm/L or greater [see Warnings and Precautions (5.4)].
- Do not administer Dextrose Injection (5%) simultaneously with blood products through the same administration set because of the possibility of pseudoagglutination or hemolysis.
- Use of a final filter is recommended during administration of parenteral solutions, where possible.
- Discard the unused portion.
- Do not use the Dextrose Injection (5%) ADD-VantageTM diluent containers with chemotherapy agents.

2.2 Important Preparation Information

Visually inspect the Dextrose Injection (5%) for particulate matter and discoloration. Do not administer Dextrose Injection (5%) if the solution is cloudy, there are precipitates, and the container is damaged.

To reduce the risk of air embolism, adhere to the following preparation instructions for Dextrose Injection (5%):

- Use a non-vented infusion set or close the vent on a vented set.
- Use a dedicated line without any connections (do not connect flexible containers in series).
- Do not pressurize the flexible container to increase flow rates.
- If using a pumping device to administer Dextrose Injection (5%), turn off the pump before the container is empty.

To Open:

- Peel overwrap at corner and remove solution container.
  - Use unit within 30 days of opening overwrap, as long as the use date does not exceed the printed expiration date.
- Some opacity of the plastic due to moisture absorption during the sterilization process may be observed. This is normal and does not affect the solution quality or safety. The opacity will diminish gradually.

To Assemble Vial and Flexible Diluent Container:

1. Remove the protective covers from the top of the vial and the vial port on the diluent container as follows:
  a. To remove the breakaway vial cap, swing the pull ring over the top of the vial and pull down far enough to start the opening (SEE FIGURE 1.), then pull straight up to remove the cap. (SEE FIGURE 2.)

NOTE: Once the breakaway cap has been removed, do not access the vial with the syringe.

  b. To remove the vial port cover, grasp the tab on the pull ring, pull up to break the three tie strings, then pull back to remove the cover. (SEE FIGURE 3.)

2. Screw the vial into the vial port until it will go no further. THE VIAL MUST BE SCREWED IN TIGHTLY TO ASSURE A SEAL. This occurs approximately 1/2 turn (180°) after the first audible click. (SEE FIGURE 4.) The clicking sound does not assure a seal; the vial must be turned as far as it will go.

NOTE: Once vial is seated, do not attempt to remove. (SEE FIGURE 4.)

3. Recheck the vial to assure that it is tight by trying to turn it further in the direction of assembly.
4. Label appropriately.

To Reconstitute the Drug:

1. Squeeze the bottom of the diluent container gently to inflate the portion of the container surrounding the end of the drug vial.
2. With the other hand, push the drug vial down into the container telescoping the walls of the container. Grasp the inner cap of the vial through the walls of the container. (SEE FIGURE 5.)
3. Pull the inner cap from the drug vial. (SEE FIGURE 6.) Verify that the rubber stopper has been pulled out, allowing the drug and diluent to mix.
4. Mix container contents thoroughly and use within the specified time.
5. Look through the bottom of the vial to verify that the stopper has been removed and complete mixing has occurred. (SEE FIGURE 7.)

If the rubber stopper is not removed from the vial, and the medication is not released on the first attempt, the inner cap may be manipulated back into the rubber stopper without removing the drug vial from the diluent container. Repeat steps 3 through 5.

Preparation for Administration:

1. Confirm the activation and admixture of vial contents.
2. Check for leaks by squeezing the container firmly. If leaks are found, discard the unit because sterility may be compromised.
3. Close the flow control clamp of the administration set.
4. Remove the cover from the outlet port at the bottom of the container.
5. Insert the piercing pin of the administration set into the port with a twisting motion until the pin is firmly seated. Note: See full directions on the administration set carton.
6. Lift the free end of the hanger loop on the bottom of the vial, breaking the two tie strings. Bend the loop outward to lock it in the upright position, then suspend the container from the hanger.
7. Squeeze and release the drip chamber to establish the proper fluid level in the chamber.
8. Open the flow control clamp and clear air from set. Close clamp.
9. Attach the set to the venipuncture device. If the device is not indwelling, prime and make venipuncture.
10. Regulate the rate of administration with the flow control clamp. Do not use the flexible container in series connections.

2.3 Dosage Considerations

The choice of dextrose concentration, rate, and volume depends on the age, weight, clinical, and metabolic conditions of the patient and concomitant therapy.

Dextrose Injection (5%) administration rate should be based on the patient’s tolerance of dextrose, especially for preterm neonates with low birth weight.

Increase the infusion rate gradually as needed; frequently monitor blood glucose concentrations to avoid hyperglycemia [see Warnings and Precautions (5.2), Use in Specific Populations (8.4)].

3 DOSAGE FORMS AND STRENGTHS

Injection:

- 5% (5 g/100 mL) (50 mg/mL) of dextrose hydrous in a clear, sterile, and nonpyrogenic solution in single-dose flexible plastic ADD-VantageTM diluent containers: 50 mL, 100 mL and 250 mL.

This dextrose product is intended to be used as a diluent for the contents of an ADD- Vantage vial or a single-dose powdered drug vial with 20 mm closure using the ADD-Vantage ADDAPTORTM.

4 CONTRAINDICATIONS

Dextrose Injection (5%) is contraindicated in patients with:

- Clinically significant hyperglycemia [see Warnings and Precautions (5.2)].
- Known hypersensitivity to dextrose [see Warnings and Precautions (5.3)].

5 WARNINGS AND PRECAUTIONS

5.1 Neonatal Hypoglycemia

Neonates, especially preterm neonates with low birth weight, are at increased risk of developing hypoglycemia. Closely monitor blood glucose concentration during treatment with Dextrose Injection (5%) to ensure adequate glycemic control in order to avoid potential long-term adverse effects.

5.2 Hyperglycemia and Hyperosmolar Hyperglycemic State

The use of Dextrose Injection (5%) in patients with impaired glucose tolerance may worsen hyperglycemia. Administration of dextrose at a rate exceeding the patient’s utilization rate may lead to hyperglycemia, coma, and death.

Hyperglycemia is associated with an increase in serum osmolality, resulting in osmotic diuresis, dehydration, and electrolyte losses [see Warnings and Precautions (5.6), Use in Specific Populations (8.4)]. Patients with underlying CNS disease and renal impairment who receive dextrose infusions may be at greater risk of developing hyperosmolar hyperglycemic state.

Monitor blood glucose levels and treat hyperglycemia to maintain levels within normal limits while administering Dextrose Injection (5%). Insulin may be administered or adjusted to maintain optimal blood glucose levels during Dextrose Injection (5%) administration.

5.3 Hypersensitivity Reactions

Hypersensitivity reactions, including anaphylaxis, have been reported with Dextrose Injection (5%) administration [see Adverse Reactions (6)]. Stop administration of Dextrose Injection (5%) immediately if signs or symptoms of a hypersensitivity reaction develop. Initiate appropriate treatment as clinically indicated.

5.4 Phlebitis and Thrombosis

The infusion of hypertonic solutions into a peripheral vein may result in vein irritation, vein damage, and/or thrombosis [see Dosage and Administration (2.1)]. If thrombophlebitis develops, remove the catheter as soon as possible.

5.5 Hyponatremia

Dextrose Injection (5%) may cause hyponatremia. Hyponatremia can lead to acute hyponatremic encephalopathy characterized by headache, nausea, seizures, lethargy, and vomiting. The risk of hospital-acquired hyponatremia is increased in younger pediatric patients, geriatric patients, patients treated with diuretics, and patients with cardiac or pulmonary failure or with the syndrome of inappropriate antidiuretic hormone (SIADH) (e.g., postoperative patients, patients concomitantly treated with arginine vasopressin analogs or certain antiepileptic, psychotropic, and cytotoxic drugs) [see Drug Interactions (7.1), Use in Specific Populations (8.4)].

Avoid Dextrose Injection (5%) in patients with or at risk for hyponatremia. If use cannot be avoided, closely monitor serum sodium concentrations, chloride concentrations, fluid status, acid-base balance, and neurologic status [see Warnings and Precautions (5.6)].

5.6 Electrolyte Imbalance and Fluid Overload

Electrolyte deficits, particularly serum potassium and phosphate, may occur during prolonged use of Dextrose Injection (5%).

Depending on the administered volume and the infusion rate, Dextrose Injection (5%) can cause fluid overload, including pulmonary edema.

Avoid Dextrose Injection (5%) in patients at risk for fluid and/or solute overload. If use cannot be avoided in these patients, monitor fluid balance, electrolyte concentrations, and acid-base balance, especially during prolonged use. Additional monitoring is recommended for patients with water and electrolyte disturbances that could be aggravated by increased glucose, insulin administration, and/or free water load.

5.7 Refeeding Syndrome

Refeeding severely undernourished patients may result in refeeding syndrome, characterized by the intracellular shift of potassium, phosphorus, and magnesium as the patient becomes anabolic. Thiamine deficiency and fluid retention may also develop. To prevent these complications, monitor severely undernourished patients and slowly increase nutrient intake.

6 ADVERSE REACTIONS

The following clinically significant adverse reactions are also described elsewhere in the labeling:

- Neonatal Hypoglycemia [see Warnings and Precautions (5.1)]
- Hyperglycemia and Hyperosmolar Hyperglycemic State [see Warnings and Precautions (5.2)]
- Hypersensitivity Reactions [see Warnings and Precautions (5.3)]
- Phlebitis and Thrombosis [see Warnings and Precautions (5.4)]
- Hyponatremia [see Warnings and Precautions (5.5)]
- Electrolyte Imbalance, Fluid Overload and Hypervolemia [see Warnings and Precautions (5.6)]
- Refeeding Syndrome [see Warnings and Precautions (5.7)]

The following adverse reactions associated with the use of Dextrose Injection (5%) were identified in clinical trials or postmarketing reports. Because some of these reactions were reported voluntarily from a population of uncertain size, it is not possible to reliably estimate their frequency or establish a causal relationship to drug exposure.

Administration site conditions: blister, erythema, extravasation, pain, phlebitis, vein damage, thrombosis

Immune system disorders: anaphylaxis, angioedema, bronchospasm, chills, hypotension, pruritus, pyrexia, rash

Cardiovascular disorders: cyanosis, volume overload

7 DRUG INTERACTIONS

7.1 Drugs with Effects on Glycemic Control and Electrolyte Balance

Dextrose Injection (5%) can affect glycemic control, vasopressin, and fluid and/or electrolyte balance [see Warnings and Precautions (5.1, 5.2, 5.5, 5.6)]. Monitor patients’ blood glucose concentrations, fluid balance, serum electrolyte concentrations, and acid-base balance.

Concomitant administration of Dextrose Injection (5%) with drugs associated with hyponatremia may increase the risk of developing hyponatremia. Drugs associated with hyponatremia include diuretics and those that cause SIADH (e.g., selective serotonin reuptake inhibitors (SSRIs), serotonin and norepinephrine reuptake inhibitors (SNRIs), arginine vasopressin analogs, certain antiepileptic, psychotropic, and cytotoxic drugs). Avoid use of Dextrose Injection (5%) in patients receiving drugs associated with hyponatremia. If use cannot be avoided, closely monitor serum sodium concentrations during concomitant use [see Warnings and Precautions (5.5)].

8 USE IN SPECIFIC POPULATIONS

8.1 Pregnancy

Risk Summary

Dextrose Injection (5%) has been used for decades during labor and delivery. Although there are a few case reports that describe adverse effects of dextrose use in other stages of pregnancy, exposure during pregnancy in general is not expected to cause major birth defects, miscarriage, or adverse maternal or fetal outcomes. Animal reproduction studies have not been conducted with dextrose.

The background risk of major birth defects and miscarriage for the indicated populations are unknown. All pregnancies have a background risk of birth defect, loss, or other adverse outcomes. In the U.S. general population, the estimated background risk of major birth defects and miscarriage in clinically recognized pregnancies is 2 to 4% and 15 to 20%, respectively.

8.2 Lactation

Risk Summary

Dextrose Injection (5%) has been used for decades and is not expected to cause harm to a breastfed infant. There are no data on the effects of Dextrose Injection (5%) on levels of glucose in human milk, on the breastfed infant, or on milk production. The developmental and health benefits of breastfeeding should be considered along with the mother’s clinical need for Dextrose Injection (5%) and any potential adverse effects on the breastfed infant from Dextrose Injection (5%) or from the underlying maternal condition.

8.4 Pediatric Use

Dextrose Injection (5%) is indicated in pediatric patients as a source of water and calories, and may also be used as a diluent for reconstitution of a powder or liquid drug product.

Neonates, especially preterm neonates with low birth weight, are at increased risk of developing hypo- or hyperglycemia. Therefore, they need close monitoring during treatment with intravenous glucose infusions to ensure adequate glycemic control in order to avoid potential long-term adverse effects.

Dextrose Injection (5%) can cause imbalances in fluid and electrolytes in pediatric patients and requires close monitoring of volume status and plasma electrolyte concentrations, particularly in pediatric patients who may have impaired ability to regulate fluids and electrolytes. Pediatric patients are at increased risk for developing hyponatremic encephalopathy [see Warnings and Precautions (5.5, 5.6)].

In very low birth weight neonates, excessive or rapid administration of Dextrose Injection (5%) may increase the risk of intracerebral hemorrhage.

8.5 Geriatric Use

Dextrose Injection (5%) has not been studied in sufficient number of patients aged 65 and over to determine whether they respond differently from younger patients. Geriatric patients are at increased risk of developing hyponatremia and hyponatremic encephalopathy [see Warnings and Precautions (5.5)]. Other reported clinical experience has not identified differences in responses between the geriatric and younger adult patients. In general, the infusion rate for geriatric patients should start slow and be titrated up cautiously, reflecting their greater risk for electrolyte abnormalities and fluid overload.

Dextrose is known to be substantially excreted by the kidney, and the risk of adverse reactions to Dextrose Injection (5%) may be greater in patients with impaired renal function. Because geriatric patients are more likely to have impaired renal function, care should be taken in selection of the infusion rate, and patients should be closely monitored during Dextrose Injection (5%) treatment.

10 OVERDOSAGE

A medication error resulting in a high infusion rate of Dextrose Injection (5%) can cause hyperglycemia, hyperosmolality, and adverse effects on fluid and electrolyte balance [see Warnings and Precautions (5.2, 5.6)].

Severe hyperglycemia and severe dilutional hyponatremia, and their complications, can be fatal. In the event of overdosage (overhydration or solute overload) during Dextrose Injection (5%) treatment, discontinue the infusion. Institute corrective measures such as administration of exogenous insulin, and treat adverse effects on the CNS, respiratory, and cardiovascular systems [see Warnings and Precautions (5.2, 5.6)].

11 DESCRIPTION

Dextrose, USP is chemically designated D-glucose, monohydrate (C6H12O6 • H2O), a hexose sugar freely soluble in water.

The molecular weight of dextrose (D-glucose) monohydrate is 198.17. It has the following structural formula:

Water for Injection, USP is chemically designated H2O.

Dextrose Injection, USP (5%) is a clear, sterile, non-pyrogenic solutions of Dextrose, USP in Water for Injection in a polyvinylchloride flexible plastic container for intravenous administration after admixture with a single-dose powdered or liquid (up to 10 mL) drug vial [see Dosage and Administration (2.1)].

Partial-fill containers, designed to facilitate admixture, are available in 50 mL, 100 mL, and 250 mL sizes. See Table 1 for the content and characteristics of this solution.

The solution contains no bacteriostatic, antimicrobial agent or added buffer and is supplied as single-dose containers. The pH is 4.3 (range is 3.2 to 6.5).

Table 1. Contents and Characteristics of 5% Dextrose Injections, USP
Strength | Fill Volume | Amount of Dextrose Hydrous per Container | kcal [Caloric value calculated on the basis of 3.4 kcal/g of dextrose, hydrous] per Container | mOsmol per Liter
5% Dextrose Injection, USP (50 mg/mL) | 50 mL | 2.5 grams | 8.5 | 253
5% Dextrose Injection, USP (50 mg/mL) | 100 mL | 5 grams | 17 | 253
5% Dextrose Injection, USP (50 mg/mL) | 250 mL | 12.5 grams | 42.5 | 253

Dextrose is derived from corn.

Exposure to temperatures above 25°C/77°F during transport and storage will lead to minor losses in moisture content. Higher temperatures lead to greater losses. It is unlikely that these minor losses will lead to clinically significant changes within the expiration period.

12 CLINICAL PHARMACOLOGY

12.1 Mechanism of Action

Dextrose provides a source of carbohydrate calories and is used to supplement nutrition by providing glucose parenterally.

12.2 Pharmacodynamics

The exposure-response relationship and time course of pharmacodynamic response for the safety and effectiveness of dextrose have not been fully characterized.

12.3 Pharmacokinetics

Dextrose is oxidized to carbon dioxide and water.

13 NONCLINICAL TOXICOLOGY

13.1 Carcinogenesis, Mutagenesis, Impairment of Fertility

Studies with dextrose to evaluate the drug’s carcinogenic potential, mutagenic potential, or effects on fertility have not been performed.

16 HOW SUPPLIED/STORAGE AND HANDLING

Dextrose Injection, USP (5%) is a clear, colorless, sterile solution of dextrose supplied in single-dose flexible plastic ADD-VantageTM diluent containers. This dosage form is intended to be used as a diluent for the contents of an ADD-Vantage vial or a single-dose powdered drug vial with a 20 mm closure using the ADD-Vantage ADDAPTORTM.

Unit of Sale | Strength | Volume
NDC 0409-7100-66 Case of 50 – 50 mL bags | 5% (2.5 g/50 mL) (50 mg/mL) | 50 mL bags
NDC 0409-7100-67 Case of 50 – 100 mL bags | 5% (5 g/100 mL) (50 mg/mL) | 100 mL bags
NDC 0409-7100-02 Case of 24 – 250 mL bags | 5% (12.5 g/250 mL) (50 mg/mL) | 250 mL bags

Do not remove the container from the overwrap until intended for use.

Use the product immediately after the introduction of additives.

Storage and Handling

Store at 20°C to 25°C (68°F to 77°F); excursions permitted between 15°C to 30°C (59°F to 86°F) [See USP Controlled Room Temperature].

Do not freeze.

To contact Pfizer’s Medical Information Department, please visit www.pfizermedinfo.com or call 1‑800-438‑1985.

Distributed by Hospira, Inc., Lake Forest, IL 60045 USA

LAB-1143-4.0

PRINCIPAL DISPLAY PANEL - 50 mL Bag Label

PULL INNER PLUG/STOPPER
AND MIX DRUG BEFORE USE

ADD-Vantage™ Unit
NDC 0409-7100-68

5% DEXTROSE
Injection, USP

50
mL

EACH 100 mL CONTAINS DEXTROSE, HYDROUS 5 g.
253 mOsmol/LITER (calc.). pH 4.3 (3.2 TO 6.5)
DEXTROSE SOLUTIONS WITHOUT SALTS SHOULD
NOT BE USED IN BLOOD TRANSFUSIONS BECAUSE
OF POSSIBLE ROULEAU FORMATION. FOR USE ONLY
WITH ADD-Vantage™ SYSTEM COMPONENTS. SINGLE-
DOSE CONTAINER. FOR IV USE. USUAL DOSAGE: SEE
PACKAGE INSERT. STERILE, NONPYROGENIC. USE ONLY
IF SOLUTION IS CLEAR AND CONTAINER IS UNDAMAGED.
MUST NOT BE USED IN SERIES CONNECTIONS.

DISTRIBUTED BY
HOSPIRA, INC.,
LAKE FOREST, IL 60045 USA

Rx ONLY
IM-4480
14475201

3
v
CONTAINS DEHP

PRINCIPAL DISPLAY PANEL - 100 mL Bag Label

PULL INNER PLUG/STOPPER
AND MIX DRUG BEFORE USE

ADD-Vantage™ Unit
NDC 0409-7100-69

5% DEXTROSE
Injection, USP

100
mL

EACH 100 mL CONTAINS DEXTROSE, HYDROUS 5 g.
253 mOsmol/LITER (calc.). pH 4.3 (3.2 TO 6.5)
DEXTROSE SOLUTIONS WITHOUT SALTS SHOULD
NOT BE USED IN BLOOD TRANSFUSIONS BECAUSE OF
POSSIBLE ROULEAU FORMATION. FOR USE ONLY WITH
ADD-Vantage™ SYSTEM COMPONENTS. SINGLE-DOSE
CONTAINER. FOR IV USE. USUAL DOSAGE: SEE PACKAGE
INSERT. STERILE, NONPYROGENIC. USE ONLY IF SOLUTION
IS CLEAR AND CONTAINER IS UNDAMAGED. MUST NOT
BE USED IN SERIES CONNECTIONS.

DISTRIBUTED BY
HOSPIRA, INC.,
LAKE FOREST, IL 60045 USA

Rx ONLY
IM-4481
14475601

3
v
CONTAINS DEHP

PRINCIPAL DISPLAY PANEL - 250 mL Bag Label

LOT
EXP.

PULL INNER PLUG/STOPPER
AND MIX DRUG BEFORE USE

ADD-Vantage™ Unit
NDC 0409-7100-04

5% DEXTROSE
Injection, USP

250
mL

EACH 100 mL CONTAINS
DEXTROSE, HYDROUS 5 g.
253 mOsmol/LITER (calc).
pH 4.3 (3.2 TO 6.5)
DEXTROSE SOLUTIONS
WITHOUT SALTS SHOULD
NOT BE USED IN BLOOD
TRANSFUSIONS BECAUSE
OF POSSIBLE ROULEAU
FORMATION. FOR USE ONLY
WITH ADD-Vantage™ SYSTEM
COMPONENTS. SINGLE-
DOSE CONTAINER. FOR
INTRAVENOUS USE. USUAL
DOSAGE: SEE INSERT. STERILE,
NONPYROGENIC. USE ONLY
IF SOLUTION IS CLEAR AND
CONTAINER IS UNDAMAGED.
MUST NOT BE USED IN SERIES
CONNECTIONS.

Rx ONLY

DISTRIBUTED BY
HOSPIRA, INC.,
LAKE FOREST, IL 60045 USA

Hospira

3
v
CONTAINS DEHP

IM-4482
14475801

PRINCIPAL DISPLAY PANEL - OVERWRAP – WR-0583

One/ADD-Vantage™ Unit

TO OPEN–PEEL AT CORNER

For use only with ADD-Vantage™ system components.

The overwrap is a moisture barrier. Use unit within 30 days of opening
overwrap, as long as the use date does not exceed the printed
expiration date. Store at 20 to 25°C (68 to 77°F). [See USP Controlled
Room Temperature.] Protect from freezing. See insert.
After removing the overwrap, check for minute leaks by
squeezing container firmly. If leaks are found, discard
unit as sterility may be impaired.

Rx only
14475901

Distributed by Hospira, Inc., Lake Forest, IL 60045 USA

Hospira

WR-0583

PRINCIPAL DISPLAY PANEL - OVERWRAP – WR-0581

TO OPEN – PEEL AT NOTCH

Five/ADD-Vantage™ Units

For use only with ADD-Vantage™ system components.

The overwrap is a moisture barrier. Use units within 30 days of opening overwrap, as long as the use
date does not exceed the printed expiration date. After removing the overwrap, check for minute
leaks by squeezing container firmly. If leaks are found, discard unit as sterility may be
impaired. Store at 20 to 25°C (68 to 77°F). [See USP Controlled Room Temperature.]

Rx only
14475301

Distributed by Hospira, Inc., Lake Forest, IL 60045 USA

Hospira

WR-0581